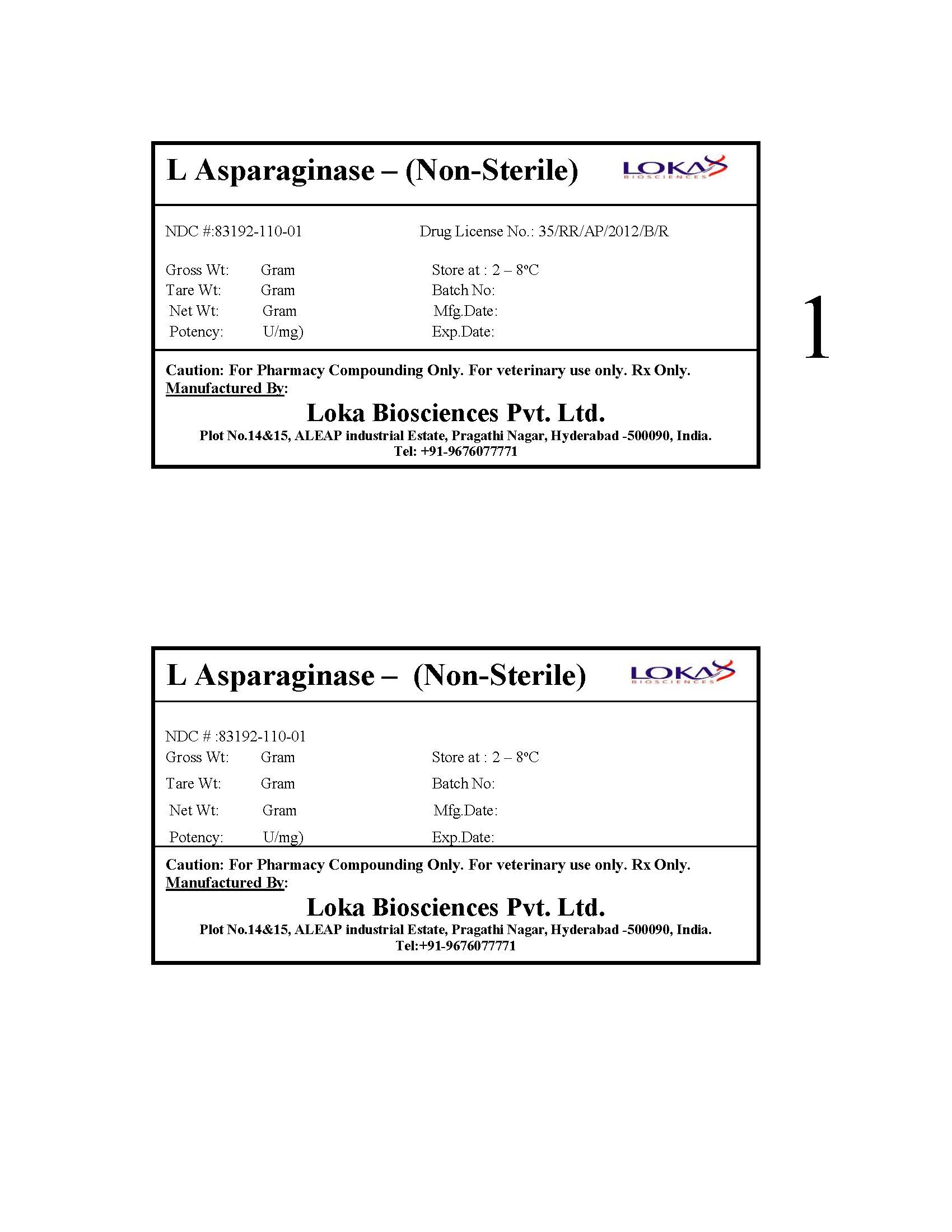 DRUG LABEL: Asparaginase
NDC: 83192-110 | Form: POWDER
Manufacturer: Loka Biosciences Pvt. Ltd
Category: other | Type: BULK INGREDIENT - ANIMAL DRUG
Date: 20230131

ACTIVE INGREDIENTS: ASPARAGINASE 1 [iU]/1 [iU]

L-Asparaginase